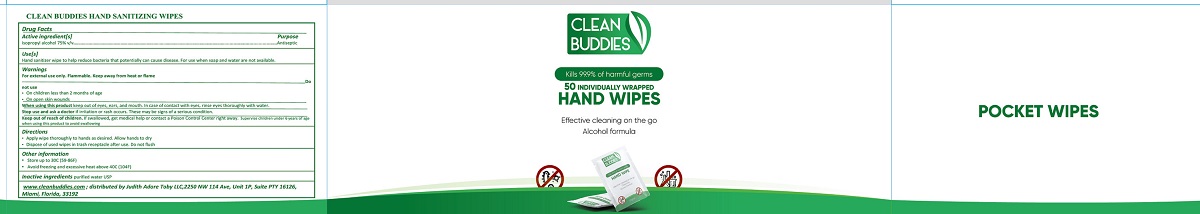 DRUG LABEL: Isopropyl alcohol 75%
NDC: 77658-001 | Form: CLOTH
Manufacturer: JUDITH ADORE TOBY LLC
Category: otc | Type: HUMAN OTC DRUG LABEL
Date: 20251218

ACTIVE INGREDIENTS: ISOPROPYL ALCOHOL 7.5 mL/1 1
INACTIVE INGREDIENTS: WATER

Active Ingredient

Isopropyl Alcohol 75% v/v.

Purpose

Antiseptic

Use[s]

Hand sanitizer wipe to help reduce bacteria that potentially can cause disease. For use when soap and water are not available.

Warnings

For external use only. Flammable. Keep away from heat or flame

Do not use

- On children less than 2 months of age
- On open skin wounds

When using this productkeep out of eyes, ears, and mouth. In case of contact with eyes, rinse eyes thoroughly with water.

Stop use and aska doctor if irritation or rash occurs. These may be signs of a serious condition.

If swallowed, get medical help or contact a Poison Control Center right away.

Keep out of reach of children. If swallowed, get medical help or contact a Poison Control Center right away.Supervise children under 6 years of

age when using this product to avoid swallowing

Directions

- Apply wipe thoroughly to hands as desired. Allow hands to dry
- Dispose of used wipes in trash receptacle after use. Do not flush

Other information

- Store up to 30C (59-86F)
- Avoid freezing and excessive heat above 40C (104F)

Inactive ingredients

Purified water USP